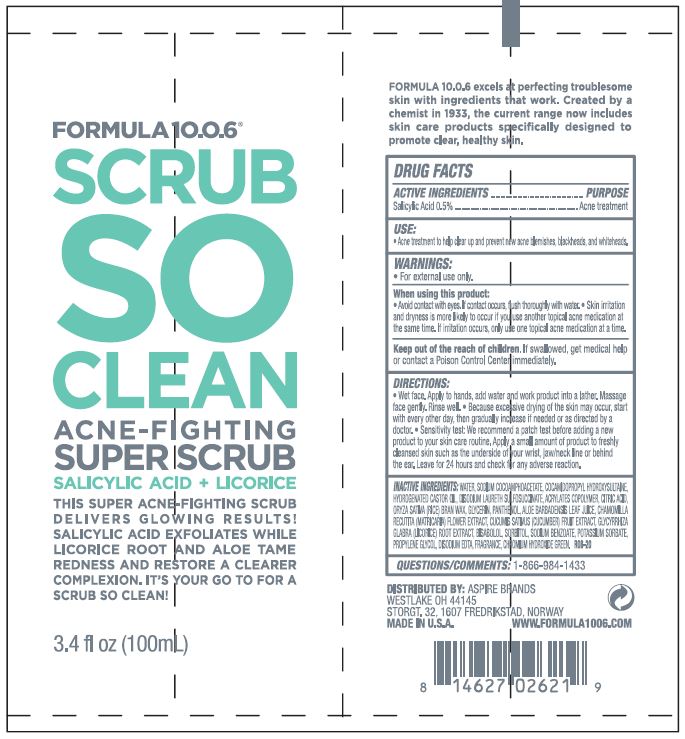 DRUG LABEL: SCRUB SO CLEAN ACNE-FIGHTING SUPER SCRUB
NDC: 70626-107 | Form: GEL
Manufacturer: ASPIRE BRANDS INC
Category: otc | Type: HUMAN OTC DRUG LABEL
Date: 20241206

ACTIVE INGREDIENTS: SALICYLIC ACID 0.5 g/100 mL
INACTIVE INGREDIENTS: WATER; SODIUM COCOAMPHOACETATE; COCAMIDOPROPYL HYDROXYSULTAINE; HYDROGENATED CASTOR OIL; DISODIUM LAURETH SULFOSUCCINATE; BUTYL ACRYLATE/METHYL METHACRYLATE/METHACRYLIC ACID COPOLYMER (18000 MW); ANHYDROUS CITRIC ACID; RICE BRAN; GLYCERIN; PANTHENOL; ALOE VERA LEAF; CHAMOMILE; CUCUMBER; GLYCYRRHIZA GLABRA; LEVOMENOL; SORBITOL; SODIUM BENZOATE; POTASSIUM SORBATE; PROPYLENE GLYCOL; EDETATE DISODIUM; CHROMIUM HYDROXIDE GREEN

ASPIRE BRANDS - FORMULA 10.0.6 SCRUB SO CLEAN ACNE-FIGHTING SUPER SCRUB (70626-107)

ACTIVE INGREDIENT

SALICYLIC ACID 0.5%

PURPOSE

ACNE TREATMENT

USE

ACNE TREATMENT TO HELP CLEAR UP AND PREVENT NEW ACNE BLEMISHES, BLACKHEADS, AND WHITEHEADS.

WARNINGS

- FOR EXTERNAL USE ONLY

WHEN USING THIS PRODUCT:

- AVOID CONTACT WITH EYES. IF CONTACT OCCURS, FLUSH THOROUGHLY WITH WATER.
- SKIN IRRITATION AND DRYNESS IS MORE LIKELY TO OCCUR IF YOU USE ANOTHER TOPICAL ACNE MEDICATION AT THE SAME TIME. IF IRRITATION OCCURS, ONLY USE ONE TOPICAL ACNE MEDICATION AT A TIME.

KEEP OUT OF REACH OF CHILDREN. IF SWALLOWED, GET MEDICAL HELP OR CONTACT A POISON CONTROL CENTER RIGHT AWAY.

DIRECTIONS

- WET FACE. APPLY TO HANDS, ADD WATER AND WORK PRODUCT INTO A LATHER. MASSAGE FACE GENTLY. RINSE WELL.
- BECAUSE EXCESSIVE DRYING OF THE SKIN MAY OCCUR, START WITH ONCE A DAY, THEN GRADUALLY INCREASE TO TWO TIMES DAILY IF NEEDED OR AS DIRECTED BY A DOCTOR.
- SENSITIVITY TEST: WE RECOMMEND A PATCH TEST BEFORE ADDING A NEW PRODUCT TO YOUR SKIN CARE ROUTINE. APPLY A SMALL AMOUNT OF PRODUCT TO FRESHLY CLEANSED SKIN SUCH AS THE UNDERSIDE OF YOUR WRIST, JAW/NECK LINE OR BEHIND THE EAR. LEAVE FOR 24 HOURS AND CHECK FOR ANY ADVERSE REACTION.

INACTIVE INGREDIENTS

WATER, SODIUM COCOAMPHOACETATE, COCAMIDOPROPYL HYDROXYSULTAINE, HYDROGENATED CASTOR OIL, DISODIUM LAURETH SULFOSUCCINATE, ACRYLATES COPOLYMER, CITRIC ACID, ORYZA SATIVA (RICE) BRAN WAX, GLYCERIN, PANTHENOL, ALOE BARBADENSIS LEAF JUICE, CHAMOMILLA RECUTITA (MATRICARIA) FLOWER EXTRACT, CUCUMIS SATIVA (CUCUMBER) FRUIT EXTRACT, GLYCYRRHIZA GLABRA (LICORICE) ROOT EXTRACT, BISABOLOL, SORBITOL, SODIUM BENZOATE, POTASSIUM SORBATE, PROPYLENE GLYCOL, DISODIUM EDTA, FRAGRANCE, CHROMIUM HYDROXIDE GREEN.

QUESTIONS/COMMENTS:

1-866-984-1433